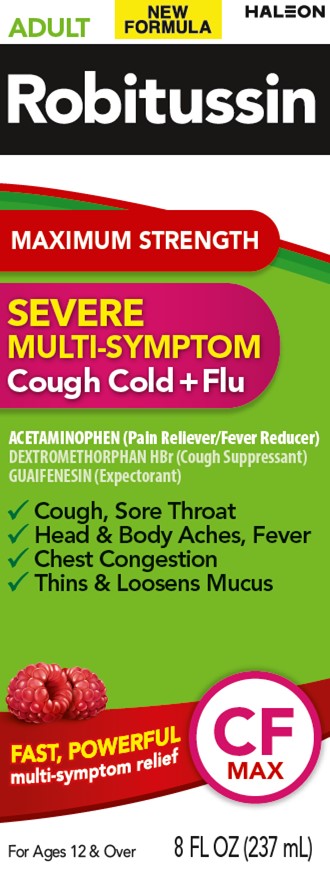 DRUG LABEL: Robitussin Maximum Strength Severe Multi-Symptom Cough Cold Flu
NDC: 0031-0100 | Form: LIQUID
Manufacturer: Haleon US Holdings LLC
Category: otc | Type: HUMAN OTC DRUG LABEL
Date: 20251118

ACTIVE INGREDIENTS: ACETAMINOPHEN 650 mg/20 mL; DEXTROMETHORPHAN HYDROBROMIDE 20 mg/20 mL; GUAIFENESIN 400 mg/20 mL
INACTIVE INGREDIENTS: ANHYDROUS CITRIC ACID; EDETATE DISODIUM; FD&C RED NO. 40; GLYCERIN; MENTHOL, UNSPECIFIED FORM; POLYETHYLENE GLYCOL, UNSPECIFIED; PROPYL GALLATE; PROPYLENE GLYCOL; WATER; SODIUM BENZOATE; SODIUM CITRATE, UNSPECIFIED FORM; SORBITOL; SUCRALOSE; TRIACETIN; XANTHAN GUM

Drug Facts

Active ingredients (in each 20 mL)

Acetaminophen 650 mg

Dextromethorphan HBr 20 mg

Guaifenesin 400 mg

Purposes

Pain reliever/Fever reducer

Cough suppressant

Expectorant

Uses

- temporarily relieves these symptoms occurring with a cold or flu:
  - cough due to minor throat and bronchial irritation
  - minor aches and pains
  - sore throat
  - headache
- temporarily reduces fever
- helps loosen phlegm (mucus) and thin bronchial secretions to drain bronchial tubes and make coughs more productive

Warnings

Liver warning:

This product contains acetaminophen. Severe liver damage may occur if you take

- more than 6 doses in any 24-hour period, which is the maximum daily amount
- with other drugs containing acetaminophen
- 3 or more alcoholic drinks every day while using this product

Allergy alert:Acetaminophen may cause severe skin reactions. Symptoms may include:

- skin reddening
- blisters
- rash

If a skin reaction occurs, stop use and seek medical help right away.

Sore throat warning

If sore throat is severe, persists for more than 2 days, is accompanied or followed by fever, headache, rash, nausea, or vomiting, consult a doctor promptly.

Do not use

- if you are now taking a prescription monoamine oxidase inhibitor (MAOI) (certain drugs for depression, psychiatric, or emotional conditions, or Parkinson's disease), or for 2 weeks after stopping the MAOI drug. If you do not know if your prescription drug contains an MAOI, ask a doctor or pharmacist before taking this product.
- with any other drug containing acetaminophen (prescription or nonprescription). If you are not sure whether a drug contains acetaminophen, ask a doctor or pharmacist.

Ask a doctor before use if you have

- liver disease
- cough that occurs with too much phlegm (mucus)
- a breathing problem or chronic cough that lasts or as occurs with smoking, asthma, chronic bronchitis, or emphysema

Ask a doctor or pharmacist before use if you are

- taking the blood thinning drug warfarin
- taking any other pain reliever/fever reducer

Stop use and ask a doctor if

- pain or cough gets worse or lasts more than 7 days
- fever gets worse or lasts more than 3 days
- redness or swelling is present
- new symptoms occur
- cough comes back or occurs with rash or headache that lasts.
  These could be signs of a serious condition.

PREGNANCY OR BREAST FEEDING

If pregnant or breast-feeding,ask a health professional before use.

Keep out of reach of children.In case of overdose, get medical help or contact a Poison Control Center right away. Prompt medical attention is critical for adults as well as for children, even if you do not notice any signs or symptoms.

Directions

- do not take more than 6 doses in any 24-hour period
- do not exceed recommended dosage. Taking more than the recommended dose (overdose) may cause serious liver damage.
- measure only with dosing cup provided
- keep dosing cup with product
- mL = milliliter
- this adult product is not intended for use in children under 12 years of age

age | dose
adults and children 12 years and over | 20 mL every 4 hours
children under 12 years | do not use

Other information

- each 20 mL contains:sodium 14 mg
- store at 20-25°C (68-77°F)

Inactive ingredients

anhydrous citric acid, edetate disodium, FD&C red no. 40, glycerin, menthol, natural and artificial flavors, polyethylene glycol, propyl gallate, propylene glycol, purified water, sodium benzoate, sodium citrate, sorbitol solution, sucralose, triacetin, xanthan gum

Questions or comments?

call weekdays from 8 AM to 6 PM EST at 1-800-245-1040

Additional information

Maximum Strength claim based on maximum levels of active ingredients per 4 hour dose.

ADULT

Robitussin

MAXIMUM STRENGTH

SEVERE MULTI-SYMPTOM

Cough Cold + Flu CF MAX

Do Not Use if breakable ring on bottle cap is separated or missing.

PARENTS:

Learn about teen medicine abuse

www.StopMedicineAbuse.org

Distributed by: Haleon, Warren, NJ 07059

For most recent product information,visit www.robitussin.com

Trademarks owned or licensed by Haleon.

Pat. Info www.productpats.com

©2023 Haleon or licensor.

PRINCIPAL DISPLAY PANEL

ADULT NEW FORMULA HALEON

Robitussin

MAXIMUM STRENGTH

SEVERE
MULTI-SYMPTOM
Cough Cold + Flu

ACETAMINOPHEN (Pain Reliever/Fever Reducer)
DEXTROMETHORPHAN HBr (Cough Suppressant)
GUAIFENESIN (Expectorant)

✓Cough, Sore Throat
✓Head & Body Aches, Fever
✓Chest Congestion
✓Thins & Loosens Mucus

FAST, POWERFUL
multi-symptom relief

CF
MAX

For Ages 12 & Over
8 FL OZ (237 mL)

62000000207716 Front Carton